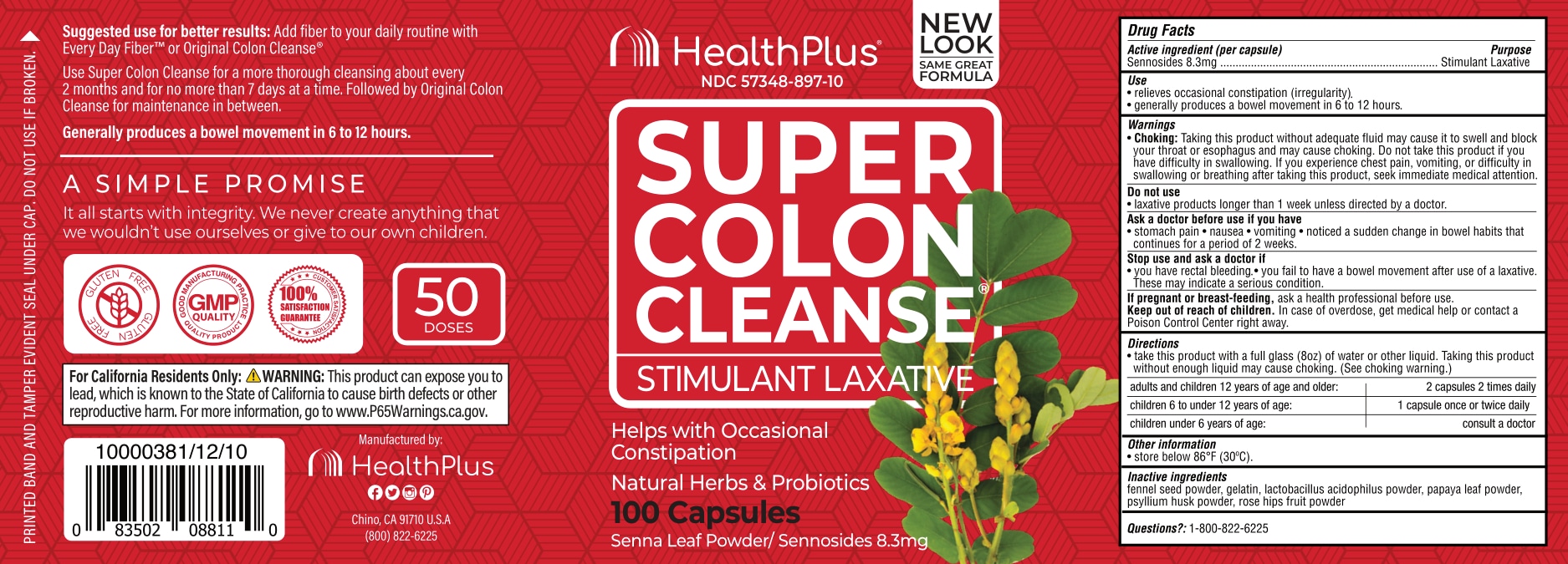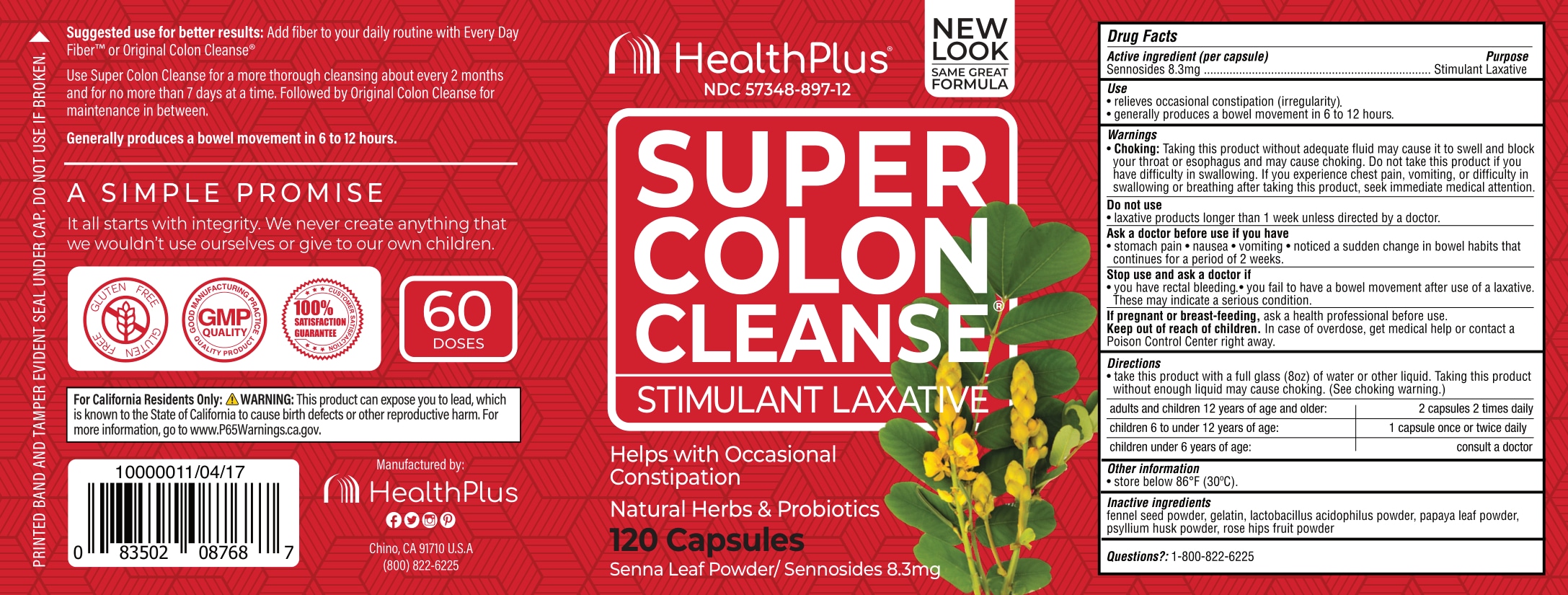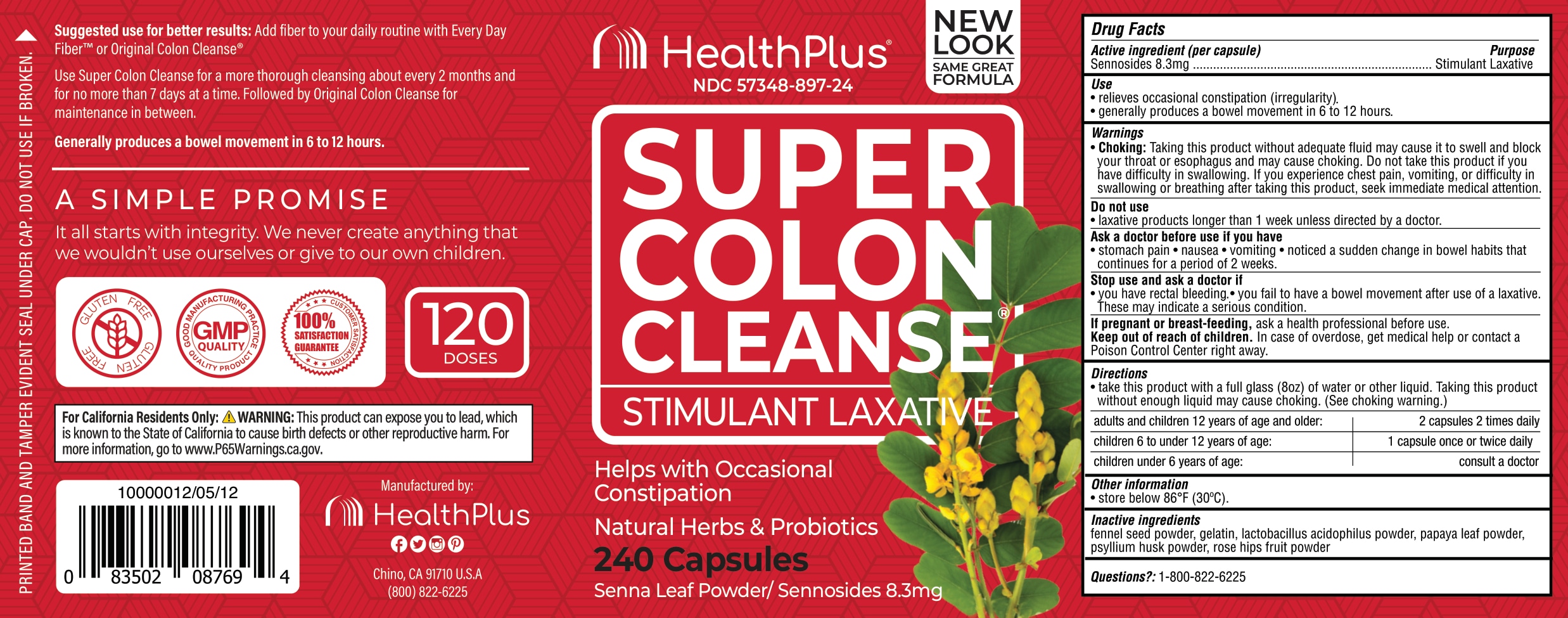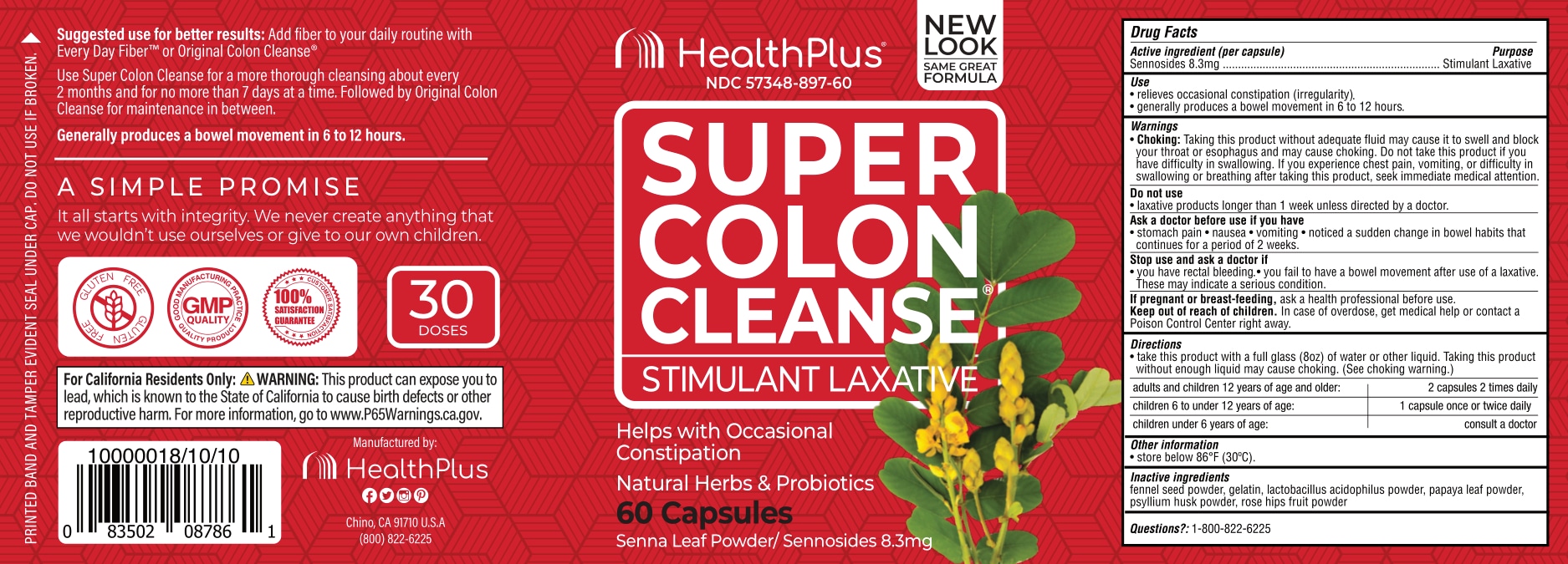 DRUG LABEL: Super Colon Cleanse
NDC: 57348-897 | Form: CAPSULE
Manufacturer: Health Plus Inc.
Category: otc | Type: HUMAN OTC DRUG LABEL
Date: 20231103

ACTIVE INGREDIENTS: SENNOSIDES 8.3 mg/1 1
INACTIVE INGREDIENTS: GELATIN, UNSPECIFIED

Super Colon Cleanse

Active ingredient (per capsulle)

Sennosides 8.3mg

Purpose

Stimulant Laxative

Use

- relieves occasional constipation (irregularity)
- generally produces a bowel movement in 6 to 12 hours

Warnings

- Choking: Taking this product without adequate fluid may cause it to swell and block your throat or esophagus and may cause choking. Do not take this product if you have difficulty in swallowing. If you experience chest pain. vomiting or difficulty in swallowing or breathing after taking this product seek immediate medical attention

Do not use

- laxative products longer than 1 week unless directed by a doctor

Ask a doctor before use if you have

• stomach pain • nausea • vomiting • noticed a sudden change in bowel habits that continues for a period of 2 weeks.

Stop use and ask a doctor if

• you have rectal bleeding • you fail to have bowel movement after use of a laxative. These may indicale a serious condition

If pregnant or breast-feeding,

• ask a health professional before use

Keep out of reach of children.

In case of overdose get medical help or contact a Poison Control Center right away

Directions

- take this product with a full glass (8oz) of water or other liquid. Taking this product without enough liquid may cause choking. (See choking warning.)

adults and children 12 years of age and older: | 2 capsules 2 times daily
children 6 to under 12 years of age: | 1 capsule once or twice daily
children under 6 years of age: | consult a doctor

Other information

• store below 86°F (30°C)

Inactive ingredients

fennel seed powder, gelatin, lactobacillus acidophilus powder, papaya leaf powder, psyllium husk powder, rose hips fruit powder

Questions?

1-800-822-6225